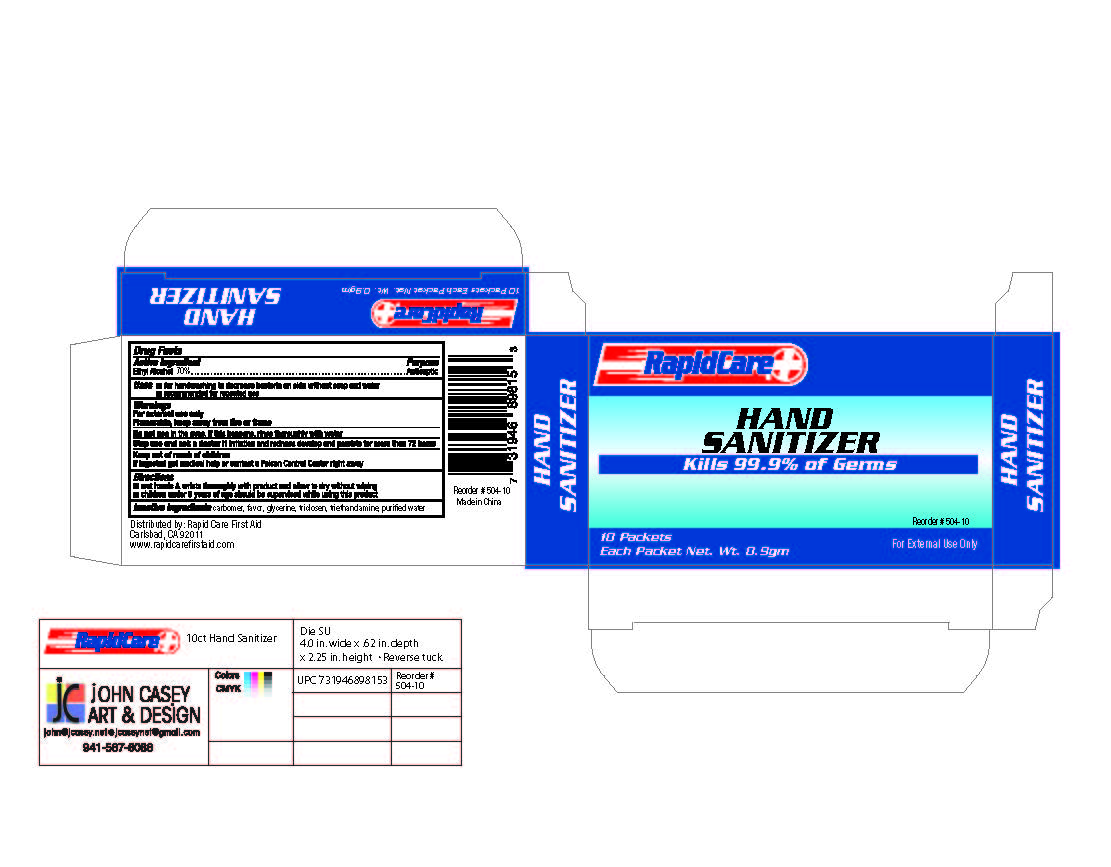 DRUG LABEL: Hand Sanitizer
NDC: 73659-004 | Form: SWAB
Manufacturer: Rapid Care, Inc
Category: otc | Type: HUMAN OTC DRUG LABEL
Date: 20211014

ACTIVE INGREDIENTS: ALCOHOL 0.7 mL/1 1
INACTIVE INGREDIENTS: TROLAMINE; WATER; TRICLOSAN; CARBOMER 940; GLYCERIN

RapidCare - Hand Sanitizer - 10pc

Active Ingredients

Alcohol 70%

Purpose

Antiseptic

Uses

- for handwashing to decrease bacteria on skin without soap and water.
- recommended for repeated use

Warnings

For external use only.

Flammable, keep away from fire or flames.

Do not use in the eyes. If this happens, rinse thoroughly with water.

Use with caution if allergic to alcohol.

Do not use

in the eyes. If this happens, rince thoroughly with water

Stop use and ask a doctor if

irritation and redness develop and persists for more than 72 hours

Keep out of reach of children.

If ingested get medical help or contact a Poison Control Center right away

Directions

- wet hands and wrists thoroughly with product and allow to dry without wiping
- children under 6 years of age should be supervised while using this product

Inactive ingredient

carbomer, favor, glycerine, triclosen, triethanolamine, purified water